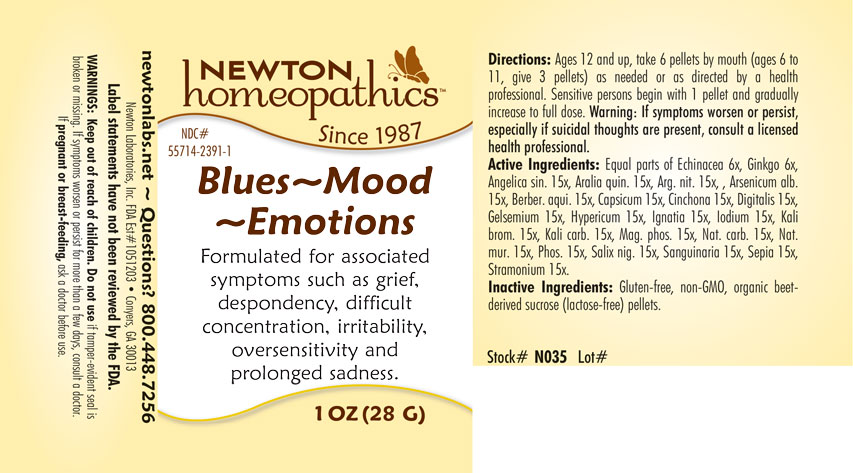 DRUG LABEL: Blues - Mood - Emotions
NDC: 55714-2391 | Form: PELLET
Manufacturer: Newton Laboratories, Inc.
Category: homeopathic | Type: HUMAN OTC DRUG LABEL
Date: 20201124

ACTIVE INGREDIENTS: ANGELICA SINENSIS ROOT 15 [hp_X]/1 g; AMERICAN GINSENG 15 [hp_X]/1 g; SILVER NITRATE 15 [hp_X]/1 g; ARSENIC TRIOXIDE 15 [hp_X]/1 g; CAPSICUM 15 [hp_X]/1 g; CINCHONA OFFICINALIS BARK 15 [hp_X]/1 g; DIGITALIS 15 [hp_X]/1 g; GELSEMIUM SEMPERVIRENS ROOT 15 [hp_X]/1 g; HYPERICUM PERFORATUM 15 [hp_X]/1 g; STRYCHNOS IGNATII SEED 15 [hp_X]/1 g; IODINE 15 [hp_X]/1 g; POTASSIUM BROMIDE 15 [hp_X]/1 g; POTASSIUM CARBONATE 15 [hp_X]/1 g; MAGNESIUM PHOSPHATE, DIBASIC TRIHYDRATE 15 [hp_X]/1 g; SODIUM CARBONATE 15 [hp_X]/1 g; SODIUM CHLORIDE 15 [hp_X]/1 g; PHOSPHORUS 15 [hp_X]/1 g; SALIX NIGRA BARK 15 [hp_X]/1 g; SANGUINARIA CANADENSIS ROOT 15 [hp_X]/1 g; SEPIA OFFICINALIS JUICE 15 [hp_X]/1 g; DATURA STRAMONIUM 15 [hp_X]/1 g; ECHINACEA, UNSPECIFIED 6 [hp_X]/1 g; GINKGO 6 [hp_X]/1 g; MAHONIA AQUIFOLIUM ROOT BARK 15 [hp_X]/1 g
INACTIVE INGREDIENTS: SUCROSE

Blues 2391P

INACTIVE INGREDIENT SECTION

Inactive Ingedients: Gluten-free, non-GMO, organc beet-derived sucrose (lactose-free) pellets.

OTC - KEEP OUT OF REACH OF CHILDREN SECTION

Keep out of reach of children.

OTC - PREGNANCY OR BREAST FEEDING SECTION

If pregnant or breast-feeding, ask a doctor before use.

WARNINGS SECTION

WARNINGS: Keep out of reach of children. Do not use if taper-evident seal is broken or missing. If symptoms worsen or persist for more than few days, consult a doctor. If pregnant or breast-feeding, ask a doctor before use.

QUESTIONS SECTION

newtonlabs.net - Questions? 800 448-7256

Newton Laboratories, Inc. FDA Est # 1051203 - Conyers, GA 30013

OTC - PURPOSE SECTION

Formulated for associated symptoms such as grief, despondency, difficult concentration, irritability, oversensitivity and prolonged sadness.

OTC - ACTIVE INGREDIENT SECTION

Equal parts of Echinacea 6x, Ginkgo 6x, Angelica sin. 15x, Aralia quin. 15x, Arg. nit. 15x, Arsenicum alb. 15x, Berber. aqui. 15x, Capsium 15x, Cinchona 15x, Digitalis 15x, Gelsemium 15x, Hypericum 15x, Ignatia 15x, Iodium 15x, Kali brom. 15x, Kali carb. 15x, Mag. phos. 15x, Nat. carb. 15x, Nat. mur. 15x, Phos. 15x, Salix nig. 15x, Sanguinaria 15x, Sepia 15x, Stramonium 15x.

DOSAGE & ADMINISTRATION SECTION

Directions: Ages 12 and up, take 6 pellets by mouth (ages 6 to 11, give 3 pellets) as needed or as directed by a health professional. Sensitive persons begin with 1 pellet and gradually increase to full dose. Warning: If symptoms worsen or persist, especially if suicidal thoughts are present, consult a licensed health professional.

INDICATIONS & USAGE SECTION

Formulated for associated symptoms such as grief, despondency, difficult concentration, irritability, oversensitivity and prolonged sadness.